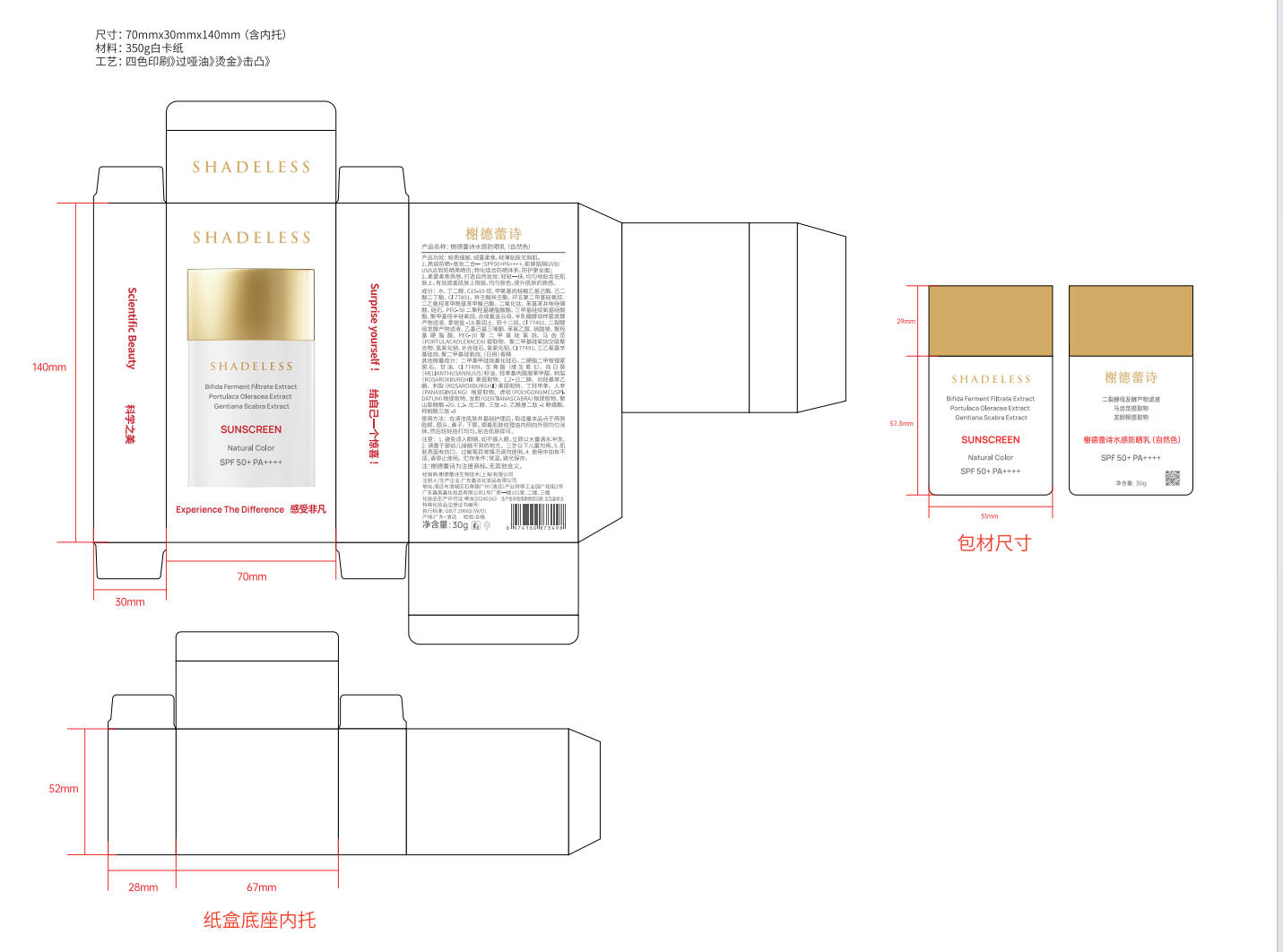 DRUG LABEL: Sunscreen SPF50
NDC: 85769-478 | Form: LOTION
Manufacturer: Guangdong Xinjie Cosmetics Co.,Ltd.
Category: otc | Type: HUMAN OTC DRUG LABEL
Date: 20251203

ACTIVE INGREDIENTS: AVOBENZONE 1 g/10 g; OCTOCRYLENE 1 g/10 g; OCTISALATE 1 g/10 g
INACTIVE INGREDIENTS: AQUA 3 g/10 g; GLYCERIN 1 g/10 g

INDICATIONS AND USAGE

Helps prevent sunburn.
If used as directed with other sun protection measures, decreases the risk of skin cancer and early skin aging caused by the sun.

PURPOSE

Sunscreen
Helps prevent sunburn

WHEN USING

• helps prevent sunburn
• if used as directed with other sun protection measures (see Directions), decreases the risk of skin cancer and early skin aging caused by the sun

WARNINGS

For external use only

Do not use
• on damaged or broken skin

When using this product
• keep out of eyes. Rinse with water to remove.

Stop use and ask a doctor if
• rash occurs

Keep out of reach of children.
If swallowed, get medical help or contact a Poison Control Center right away.

Keep out of reach of children.
If swallowed, get medical help or contact a Poison Control Center right away.

DOSAGE AND ADMINISTRATION

• Apply liberally 15 minutes before sun exposure.
• Reapply at least every 2 hours.
• Use a water-resistant sunscreen if swimming or sweating.
• Children under 6 months of age: Ask a doctor.

Sun Protection Measures:
• Spending time in the sun increases your risk of skin cancer and early skin aging.
• To decrease this risk, regularly use a sunscreen with a Broad Spectrum SPF value of 15 or higher and other sun protection measures including:
• Limit time in the sun, especially from 10 a.m. – 2 p.m.
• Wear long-sleeve shirts, pants, hats, and sunglasses.

INACTIVE INGREDIENT

Water

PACKAGE LABEL

Sunscreen SPF 50
Broad Spectrum
Water Resistant (80 minutes)
50 mL (1.69 fl oz)